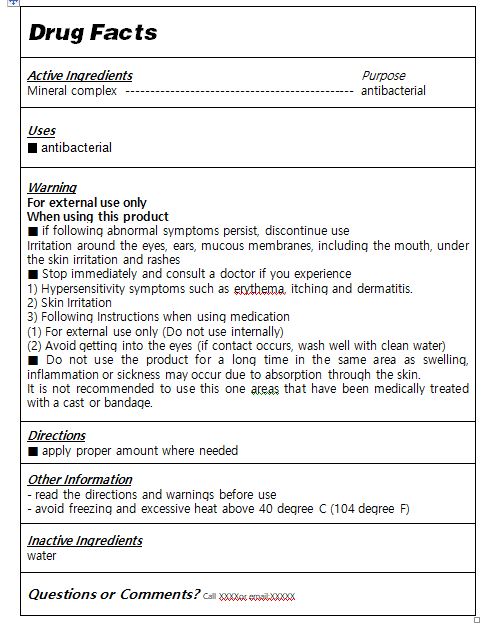 DRUG LABEL: Keeper medal
NDC: 81016-0001 | Form: LIQUID
Manufacturer: AML Bio Co., Ltd.
Category: otc | Type: HUMAN OTC DRUG LABEL
Date: 20240123

ACTIVE INGREDIENTS: MINERAL OIL 100 g/100 mL
INACTIVE INGREDIENTS: WATER

Drug Facts

ACTIVE INGREDIENT

mineral complex

PURPOSE

antiseptic

KEEP OUT OF REACH OF THE CHILDREN

INDICATIONS AND USAGE

apply proper amount to the subject area

WARNINGS

■ For external use only.

■ Do not use in eyes.

■ lf swallowed, get medical help promptly.

■ Stop use, ask doctor lf irritation occurs.

■ Keep out of reach of children.

DOSAGE AND ADMINISTRATION

for external use only

INACTIVE INGREDIENT

Water